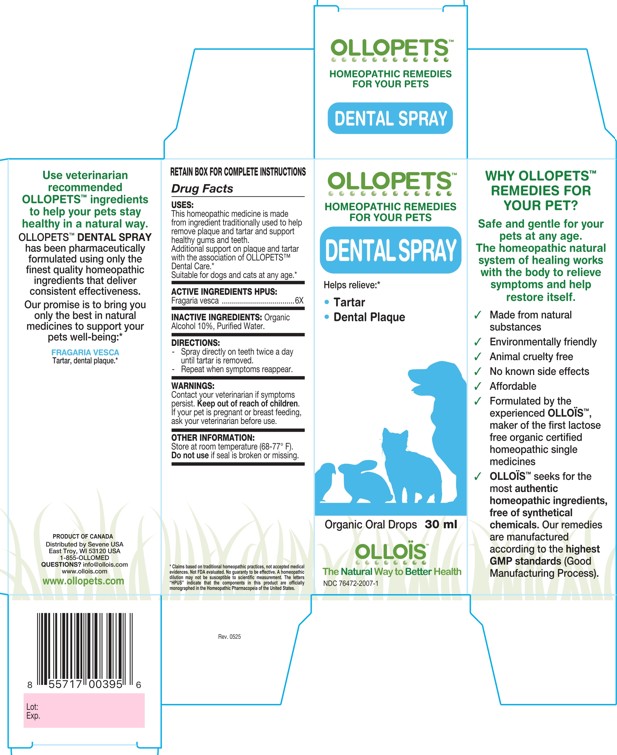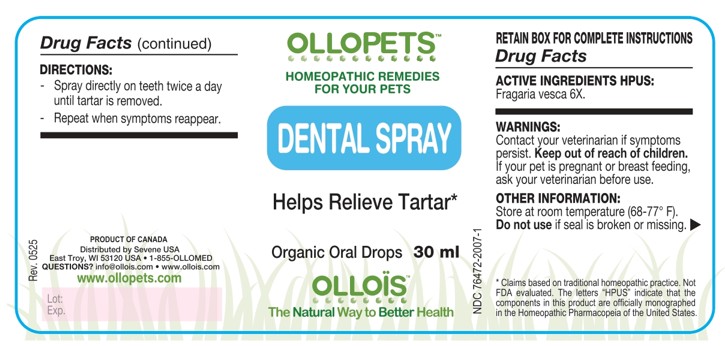 DRUG LABEL: OLLOPETS DENTAL
NDC: 76472-2007 | Form: SPRAY
Manufacturer: SEVENE USA
Category: homeopathic | Type: OTC ANIMAL DRUG LABEL
Date: 20260218

ACTIVE INGREDIENTS: FRAGARIA VESCA WHOLE 6 [hp_X]/100 mL
INACTIVE INGREDIENTS: ALCOHOL; WATER

SEVENE USA - OLLOPETS - DENTAL SPRAY

ACTIVE INGREDIENT HPUS

Fragaria vesca ....................................6X